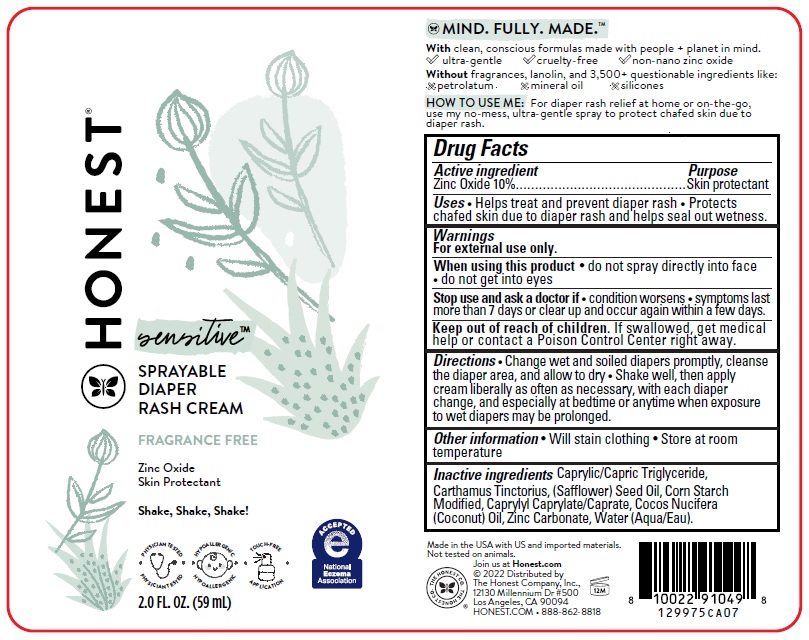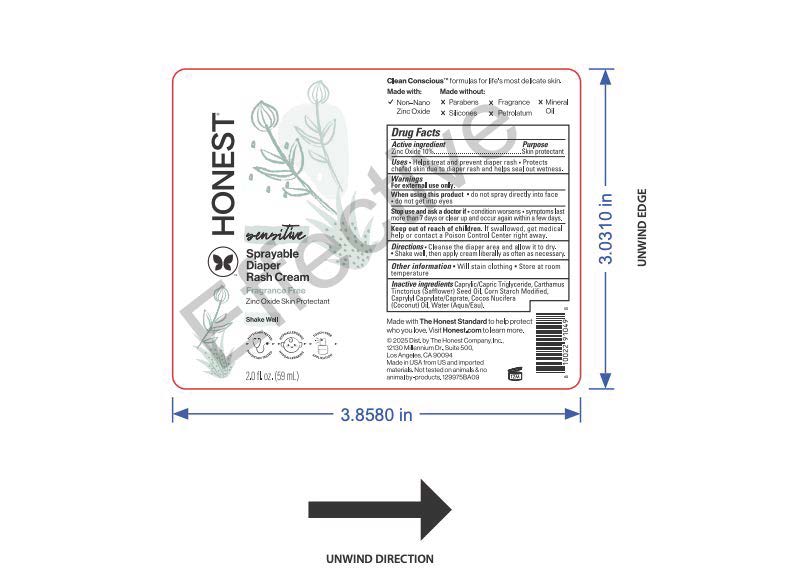 DRUG LABEL: Sprayable Diaper Rash Cream
NDC: 69366-509 | Form: SPRAY
Manufacturer: The Honest Company, Inc.
Category: otc | Type: HUMAN OTC DRUG LABEL
Date: 20251218

ACTIVE INGREDIENTS: ZINC OXIDE 10 g/100 mL
INACTIVE INGREDIENTS: SAFFLOWER OIL; MODIFIED CORN STARCH (1-OCTENYL SUCCINIC ANHYDRIDE); MEDIUM-CHAIN TRIGLYCERIDES; CAPRYLYL CAPRYLATE/CAPRATE; WATER; COCONUT OIL

Sprayable Diaper Rash Cream

Active ingredient

Zinc oxide 10%

Purpose

Skin protectant

Uses

- Helps treat and prevent diaper rash
- Protects chafed skin due to diaper rash and helps seal out wetness

Warnings

For external use only.

When using this product

- do not spray directly into face
- do not get into eyes

Stop use and ask a doctor if

- condition worsens
- symptoms last more than 7 days or clear up and occur again within a few days.

Keep out of reach of children.If swallowed, get medical help or contact a Poison Control Center right away.

Directions

- Change wet and soiled diapers promptly, cleanse the diaper area, and allow to dry
- Shake well then apply cream liberally as often as necessary, with each diaper change, and especially at bedtime or anytime when exposure to wet diapers may be prolonged.

Other information

- Will stain clothing
- Store at room temperature

INACTIVE INGREDIENT

Inactive ingredientsCaprylic/Capric Triglyceride, Carthamus Tinctorius (Safflower) Seed Oil, Corn Starch Modified, Caprylyl Caprylate/Caprate, Cocos Nucifera (Coconut) Oil, Zinc Carbonate, Water (Aqua/Eau).

Inactive ingredients

Caprylic/Capric Triglyceride, Carthamus Tinctorius (Safflower) Seed Oil, Corn Starch Modified, Caprylyl Caprylate/Caprate, Cocos Nucifera (Coconut) Oil, Water (Aqua/Eau)

PACKAGE LABEL

HONEST®

sensitive™

SPRAYABLE DIAPER RASH CREAM

FRAGRANCE FREE

Zinc Oxide

Skin Protectant

2.0 FL. OZ. (59 mL)

HOW TO USE ME: For diaper rash relief at home or on-the-go, use my no-mess, ultra-gentle spray to protect chafed skin due to diaper rash.

Made in the USA with US And imported materials.

Not tested on animals.

©2022 Distributed by

The Honest Company, Inc.

12130 Millennium Dr #500

Los Angeles, CA 90094

HONEST.COM • 888-862-8818

PACKAGE LABEL

HONEST ®

sensitive™

SPRAYABLE DIAPER RASH CREAM

FRAGRANCE FREE

Zinc Oxide

Skin Protectant

2.0 FL. OZ. (59 mL)

HOW TO USE ME: For diaper rash relief at home or on-the-go, use my no-mess, ultra-gentle spray to protect chafed skin due to diaper rash.

Made in the USA with US And imported materials.

Not tested on animals.

©2022 Distributed by

The Honest Company, Inc.

12130 Millennium Dr #500

Los Angeles, CA 90094

HONEST.COM